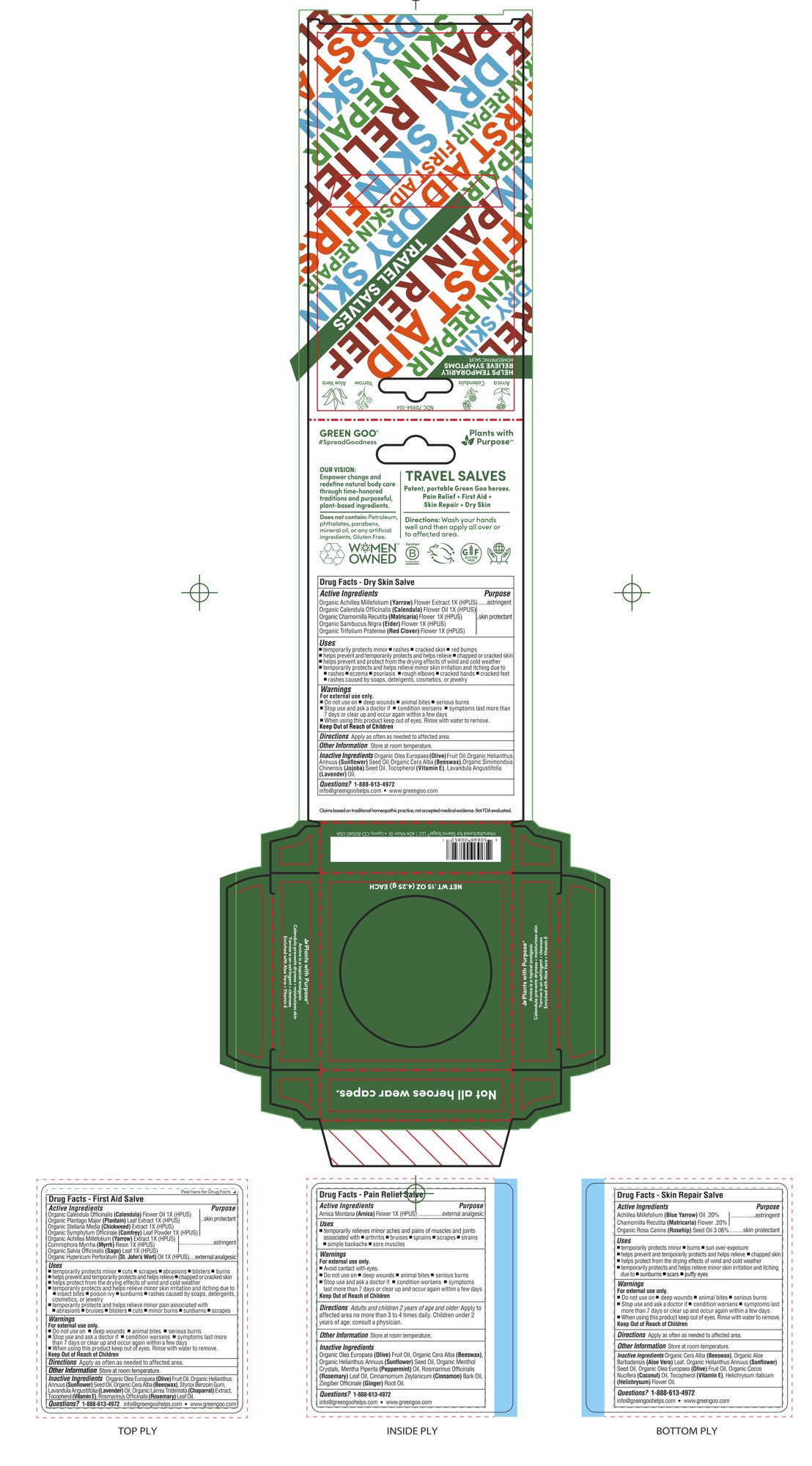 DRUG LABEL: First Aid 4pc MIni Stick Kit
NDC: 70994-104 | Form: KIT | Route: TOPICAL
Manufacturer: Spry Life LLC
Category: homeopathic | Type: HUMAN OTC DRUG LABEL
Date: 20251215

ACTIVE INGREDIENTS: ACHILLEA MILLEFOLIUM FLOWER 1 [hp_X]/51.7 g; COMMIPHORA MYRRHA WHOLE 1 [hp_X]/51.7 g; PLANTAGO MAJOR 1 [hp_X]/51.7 g; CALENDULA OFFICINALIS FLOWER 1 [hp_X]/51.7 g; STELLARIA MEDIA 1 [hp_X]/51.7 g; ST. JOHN'S WORT 1 [hp_X]/51.7 g; COMFREY LEAF 1 [hp_X]/51.7 g; SALVIA OFFICINALIS WHOLE 1 [hp_X]/51.7 g; CHAMOMILE 1 [hp_X]/51.7 g; SAMBUCUS NIGRA FLOWER 1 [hp_X]/51.7 g; TRIFOLIUM PRATENSE FLOWER 1 [hp_X]/51.7 g; ACHILLEA MILLEFOLIUM 1 [hp_X]/51.7 g; CALENDULA OFFICINALIS FLOWER 1 [hp_X]/51.7 g; ARNICA MONTANA FLOWER 1 [hp_X]/17 g; MATRICARIA RECUTITA 0.19 g/100 g; ROSA MOSCHATA OIL 3.06 g/100 g; ACHILLEA MILLEFOLIUM 0.19 g/100 g
INACTIVE INGREDIENTS: LAVENDER OIL; ROSEMARY OIL; OLIVE OIL; STYRAX BENZOIN RESIN; ALPHA-TOCOPHEROL; LARREA TRIDENTATA LEAF; YELLOW WAX; SUNFLOWER OIL; JOJOBA OIL; SUNFLOWER OIL; OLIVE OIL; LAVENDER OIL; YELLOW WAX; ALPHA-TOCOPHEROL; SUNFLOWER OIL; MENTHOL; MENTHA PIPERITA; OLIVE OIL; YELLOW WAX; CINNAMON OIL; GINGER OIL; ROSEMARY OIL; YELLOW WAX; ALOE VERA LEAF; SUNFLOWER OIL; COCONUT OIL; ALPHA-TOCOPHEROL; OLIVE OIL; HELICHRYSUM ITALICUM FLOWER OIL

First Aid 4pc Mini Stick Kit

Purpose Section

Skin Protectant

Astringent

External Analgesic

Active Ingredients

Organic Calendula Officinalis (Calendula) Flower Oil 1X (HPUS)
Organic Plantago Major (Plantain) Leaf Extract 1X (HPUS)
Organic Stellaria Media (Chickweed) Extract 1X (HPUS)
Organic Symphytum Officinale (Comfrey) Leaf Powder 1X (HPUS)

OrganicAchilleaMillefolium(Yarrow)Extract1X(HPUS)

Commiphora Myrrha (Myrrh) Resin 1X (HPUS)

Organic Salvia Officinalis (Sage) Leaf 1X (HPUS)
Organic Hypericum Perforatum (St. John’s Wort) Oil 1X (HPUS)

Indications & Usage

• temporarily protects minor • cuts • scrapes • abrasions • bruises • blisters • burns

▪︎ temporarily protects and helps relieve • chapped or cracked skin

▪︎ helps protect from the drying effects of wind and cold weather
▪︎ temporarily protects and helps relieve minor skin irritations and itching due to • insect bites • poison ivy • sunburns

• rashes caused by soaps, detergents, cosmetics, or jewelry
▪︎ temporarily protects and helps relieves minor pain associated with • abrasions • bruises • blisters • cuts • minor burns • sunburns

• scrapes

Keep out of reach of children section

Keep out of reach of children.

Warnings Section

Warnings

For external use only.

• Do not use on • deep wounds • animal bites • serious burns

• Stop use and ask a doctor if • condition worsens • symptoms last more than 7 days or clear up and occur again within a few days

• When using this product keep out of eyes. Rinse with water to remove.

Storage

Store at room temperature.

Dosage & Administration Section

Apply as often as needed to affected area.

Inactive Ingredients

Organic Olea Europaea (Olive) Fruit Oil, Organic Helianthus Annuus (Sunflower) Seed Oil, Organic Cera Alba (Beeswax), Styrax Benzoin Gum, Organic Larrea Tridentata (Chapparal) Extract, Tocopherol (Vitamin E), Lavandula Angustifolia (Lavender) Oil, Rosmarinus Officinalis (Rosemary) Leaf Oil.